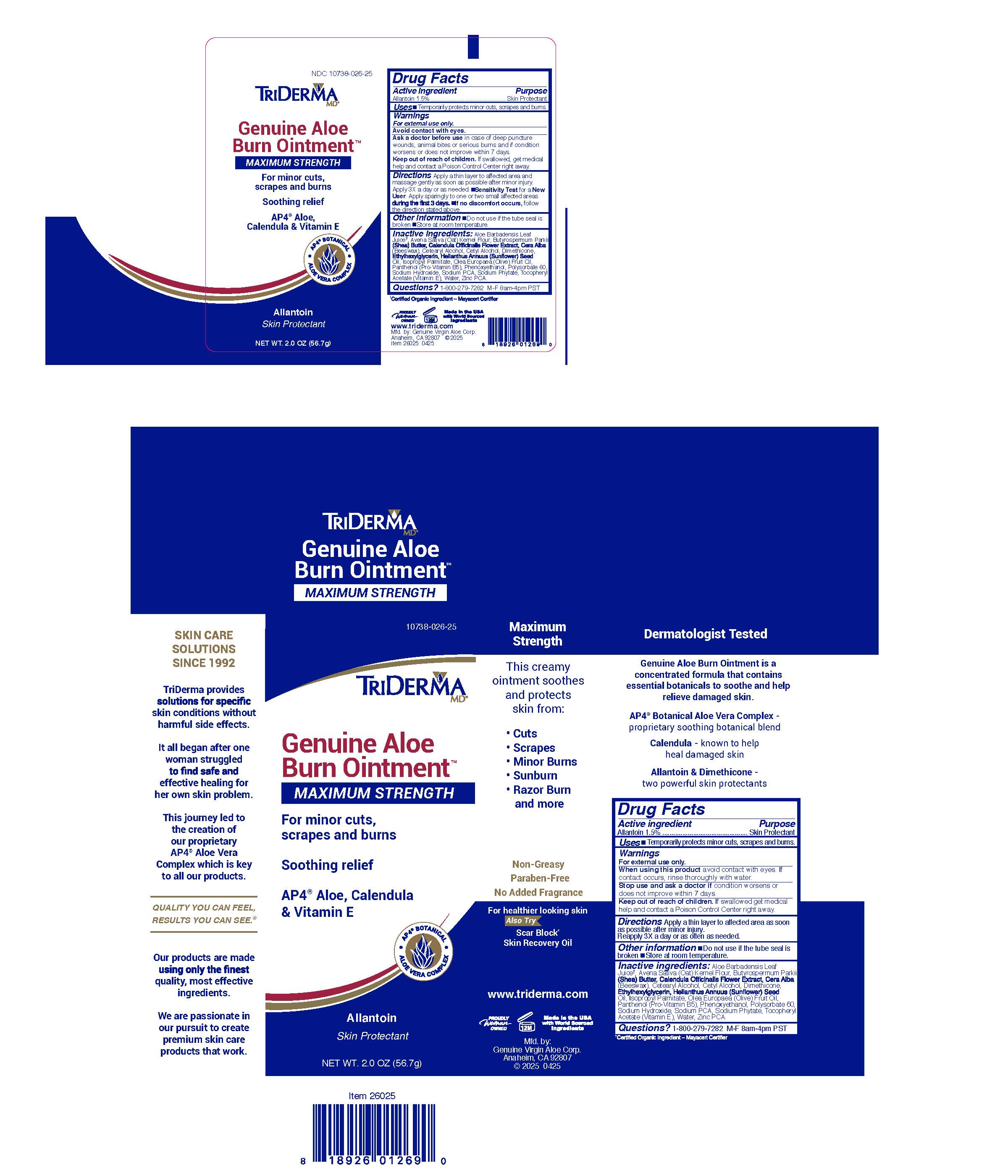 DRUG LABEL: TriDerma Genuine Aloe Burn
NDC: 10738-026 | Form: CREAM
Manufacturer: Genuine Virgin Aloe Corporation
Category: otc | Type: HUMAN OTC DRUG LABEL
Date: 20260131

ACTIVE INGREDIENTS: ALLANTOIN 1.5 g/100 g
INACTIVE INGREDIENTS: ALOE VERA LEAF JUICE; OATMEAL; SHEA BUTTER; DIMETHICONE 100; PANTHENOL; ZINC PCA

TriDerma Genuine Aloe Burn Ointment

WARNINGS

For external use only.

Active ingredient

Allantoin 1.5%

Keep out of reach of children.

If swallowed, get medical help and contact a Poison Control Center right away.

PURPOSE

Skin Protectant

QUESTIONS

1-800-279-7282 M-F 8am-4pm PST

Stop use and ask a doctor before use

in case of deep puncture wounds, animal bites or serious burns and if condition persists for more than 4 days or worsens.

WHEN USING THIS PRODUCT

avoid contact with eyes. if contact occurs, rinse thoroughly with water

INACTIVE INGREDIENTS

Aloe Barbadensis Leaf Juice†

Avena Sativa (Oat) Kernel Flour

Beeswax

Butyrospermum Parkii (Shea) Butter

Calendula Officinalis Flower Extract

Cetearyl Alcohol

Cetyl Alcohol

Dimethicone

Ethylhexylglycerin

Helianthus Annuus (Sunflower) Seed Oil

Isopropyl Palmitate

Olea Europaea (Olive) Fruit Oil

Panthenol

Phenoxyethanol

Polysorbate 60

Sodium Hydroxide

Sodium PCA

Sodium Phytate

Tocopheryl Acetate

Water (Aqua)

Zinc PCA

†Certified Organic Ingredient — Mayacert Certifier

DIRECTIONS

Apply a thin layer to affected area as soon as possible after minor injury. Reapply 3 times a day or as often as needed

USES

Temporarily protects minor cuts, scrapes and burns.